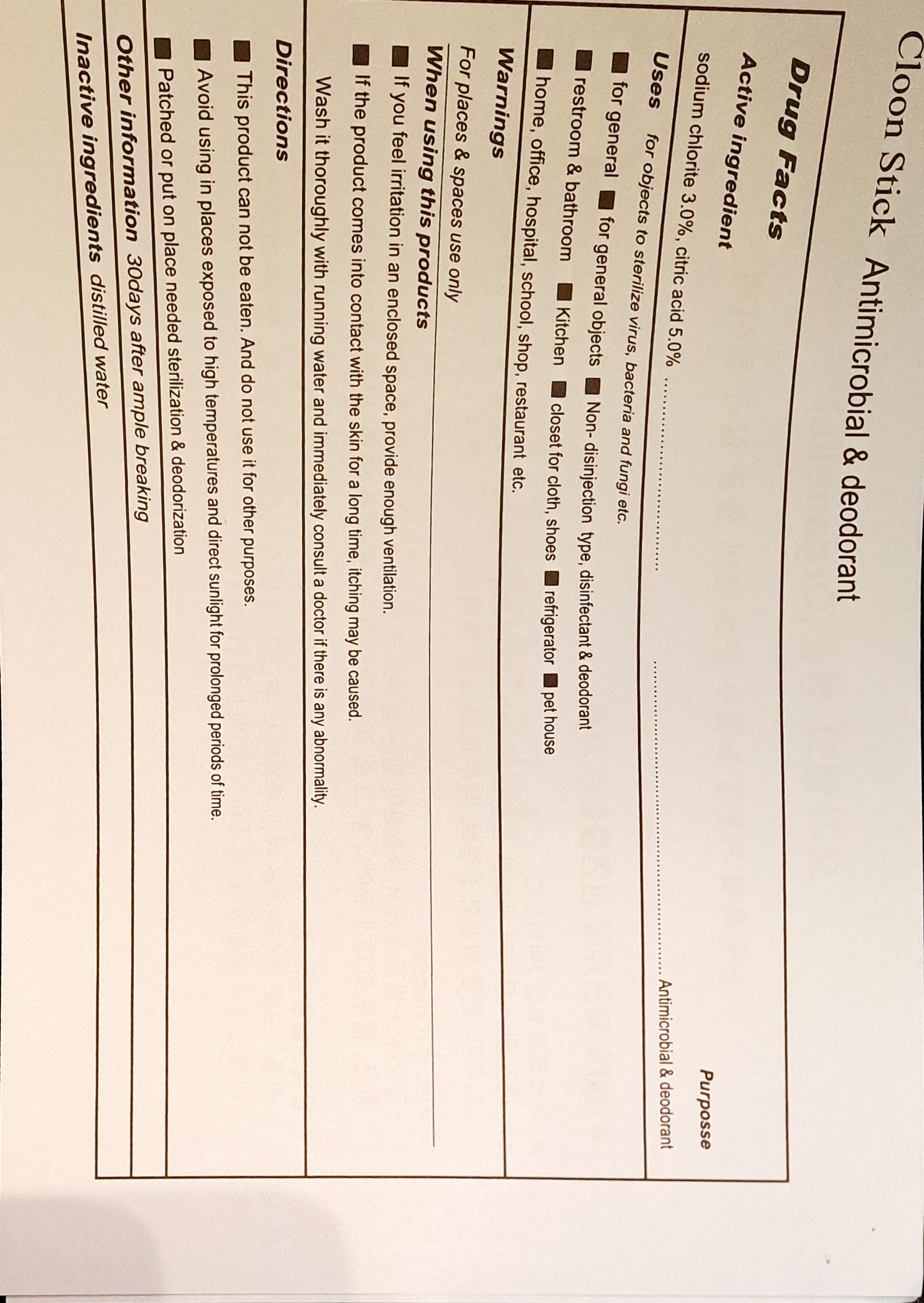 DRUG LABEL: Cloon Stick
NDC: 77130-0005 | Form: LIQUID
Manufacturer: Sejin E&P Co., Ltd.
Category: otc | Type: HUMAN OTC DRUG LABEL
Date: 20220221

ACTIVE INGREDIENTS: CITRIC ACID MONOHYDRATE 5 g/100 g; SODIUM CHLORITE 3 g/100 g
INACTIVE INGREDIENTS: WATER

Drug Facts

ACTIVE INGREDIENT

sodium chlorite, citric acid

INACTIVE INGREDIENT

water

PURPOSE

for objects to sterilize virus, bacteria and fungi etc

KEEP OUT OF REACH OF THE CHILDREN

INDICATIONS AND USAGE

This product can not be eaten. And do not use it for other purposes

Avoid using in places exposed to high temperatures and direct sunlight for prolonged periods of time.

patched or put on place needed sterilization and deodorization.

WARNINGS

If you feel irritation in an enclosed space, provide enough ventilation

If the product comes into contact with the skin for a long time, itching may be caused.
Wash it thoroughly with running water and immediately consult a doctor if there is any abnormality.

DOSAGE AND ADMINISTRATION

for keeping freshness through sterilizing and disinfecting microbial(fungi, bacteria)